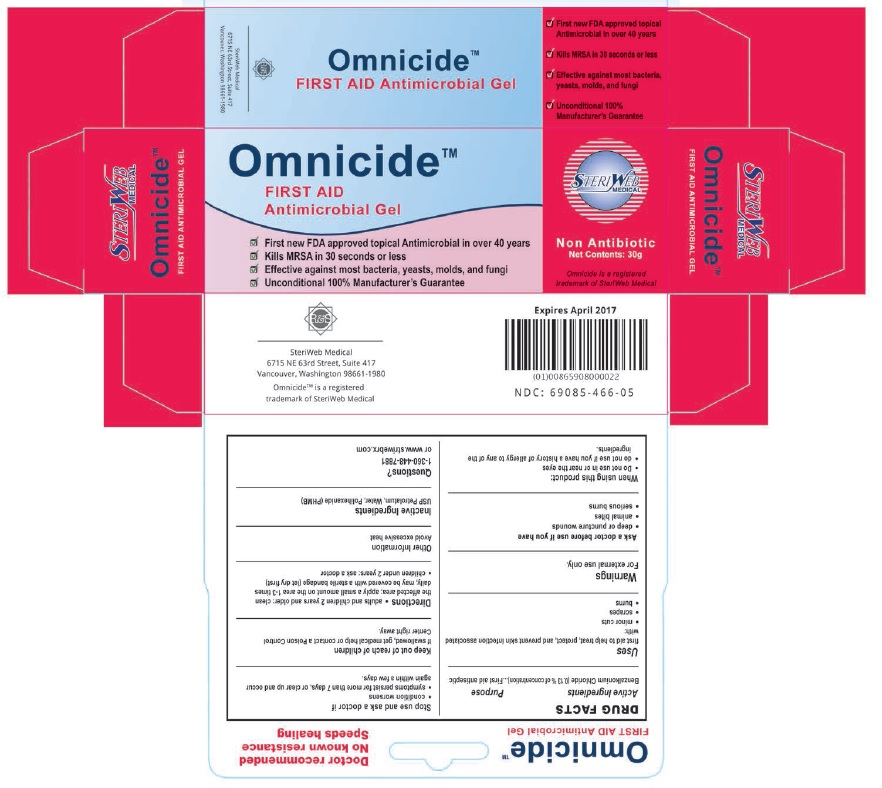 DRUG LABEL: Omnicide Antimicrobial
NDC: 69085-466 | Form: GEL
Manufacturer: SteriWeb Medical, LLC
Category: otc | Type: HUMAN OTC DRUG LABEL
Date: 20230926

ACTIVE INGREDIENTS: BENZALKONIUM CHLORIDE 0.13 g/100 g
INACTIVE INGREDIENTS: WATER; POLIHEXANIDE; PETROLATUM

STERIWEB RX (as PLD) - OMNICIDE ANTIMICROBIAL GEL (69085-466-05)

Active Ingredient

Benzalkonium Chloride 0.13% w/w

Purpose

First Aid Antiseptic

Uses

First aid to help treat, protect and prevent skin infection associated with

- minor cuts
- scrapes
- burns

Warnings

For external use only

Ask a doctor before use if you have

- deep or puncture wounds
- animal bites
- serious burns

When using this product

- Do not use in or near the eyes
- Do not use if you have a history of allergy to any of the ingredients

Stop and ask a doctor if

- condition worsens
- symptoms persist for more than 7 days, or clear up and occur again within a few days.

Keep out of reach of children.

If swallowed, get medical help or contact a Poison Control Center right away

Directions

- adults and children 2 years and older: clean the affected area; apply a small amount on the area 1-3 times daily; may be covered with a sterile bandage (let dry first)
- children under 2 years: ask a doctor

Other information

Avoid excessive heat.

Inactive Ingredients

USP Petrolatum, Water, Polihexanide (PHBM)

Questions?

1-360-448-7881

or www.steriwebrx.com